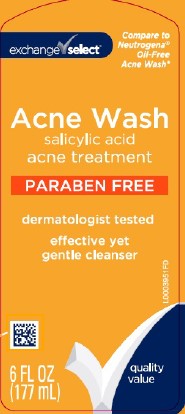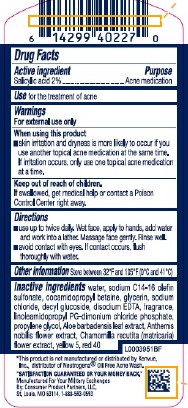 DRUG LABEL: Oil Free Acne Wash
NDC: 55301-947 | Form: LOTION
Manufacturer: Your Military Exchanges
Category: otc | Type: HUMAN OTC DRUG LABEL
Date: 20260212

ACTIVE INGREDIENTS: SALICYLIC ACID 20 mg/1 mL
INACTIVE INGREDIENTS: SODIUM C14-16 OLEFIN SULFONATE; WATER; COCAMIDOPROPYL BETAINE; GLYCERIN; SODIUM CHLORIDE; DECYL GLUCOSIDE; EDETATE DISODIUM ANHYDROUS; LINOLEAMIDOPROPYL PROPYLENE GLYCOL-DIMONIUM CHLORIDE PHOSPHATE; PROPYLENE GLYCOL; ALOE VERA LEAF; CHAMAEMELUM NOBILE FLOWER; CHAMOMILE; FD&C YELLOW NO. 5; FD&C RED NO. 40

Exchange Select 947.003/947AC-AD
Oil Free Acne Wash

Active ingredient

Salicylic acid 2%

Purpose

Acne medication

Use

for the treatment of acne

Warnings

For external use only

When using this product

- skin irritation and dryness is more likely to occur if you use another topical acne medication at the same time. If irritation occurs, only use one topical acne medication at a time

Keep out of reach of children.

If swallowed, get medical help or contact a Poison Control Center right away.

Directions

- use up to twice daily. Wet face, apply to hands, add water and work into lather. Massage face gently. Rinse well.
- avoid contact with eyes. If contact occurs, flush thoroughly with water.

Other information

Store between 32F and 105F (0C and 41C)

Inactive ingredients

water, sodium C14-16 olefin sulfonate, cocamidopropyl betaine, glycerin, sodium chloride, decyl glucoside, disodium EDTA, fragrance, linoleamidopropyl PG-dimonium chloride phosphate, propylene glycol, Aloe barbadensis leaf extract, Anthemis nobilis flower extract, Chamomilla recutita (matricaria) flower extract, yellow 5, red 40

Disclaimer

*This product is not manufactured or distributed by Kenvue, Inc., distributer of Neutrogena®Oil Free Acne Wash.

ADVERSE REACTION

"SATISFACTION GUARANTEED OR YOUR MONEY BACK."

Manufactured For Your Military Exchanges

By: Consumer Product Partners, LLC,

St. Louis, MO 63114 1-888-593-0593

Principal display panel

Compare to Neutrogena®Oil-Free Acne Wash*

exchange select™

Acne Wash

Salicylic acid

acne treatment

PARABEN FREE

dermatologist tested

effective yet gentle cleanser

quality value

6 FL OZ (177 mL)